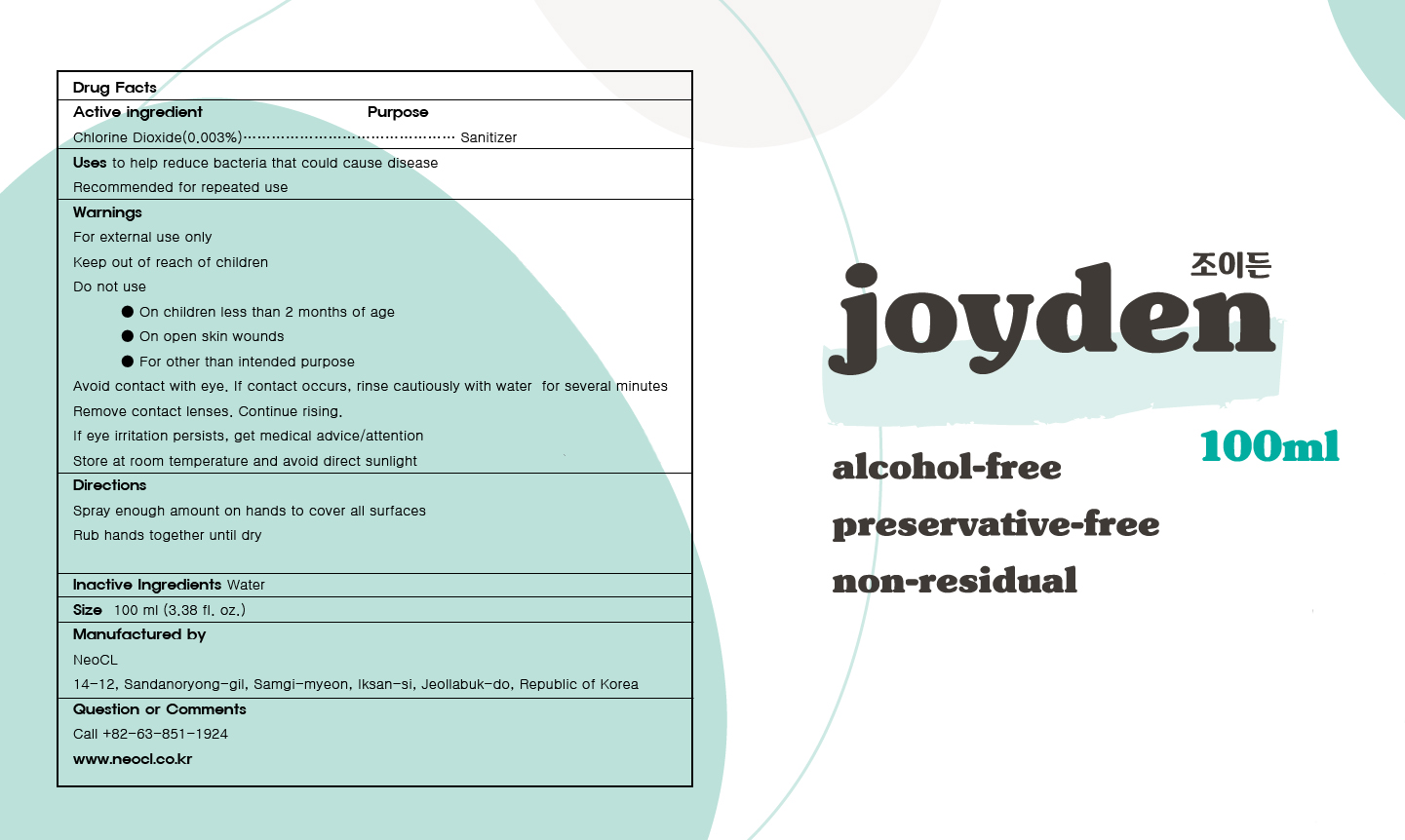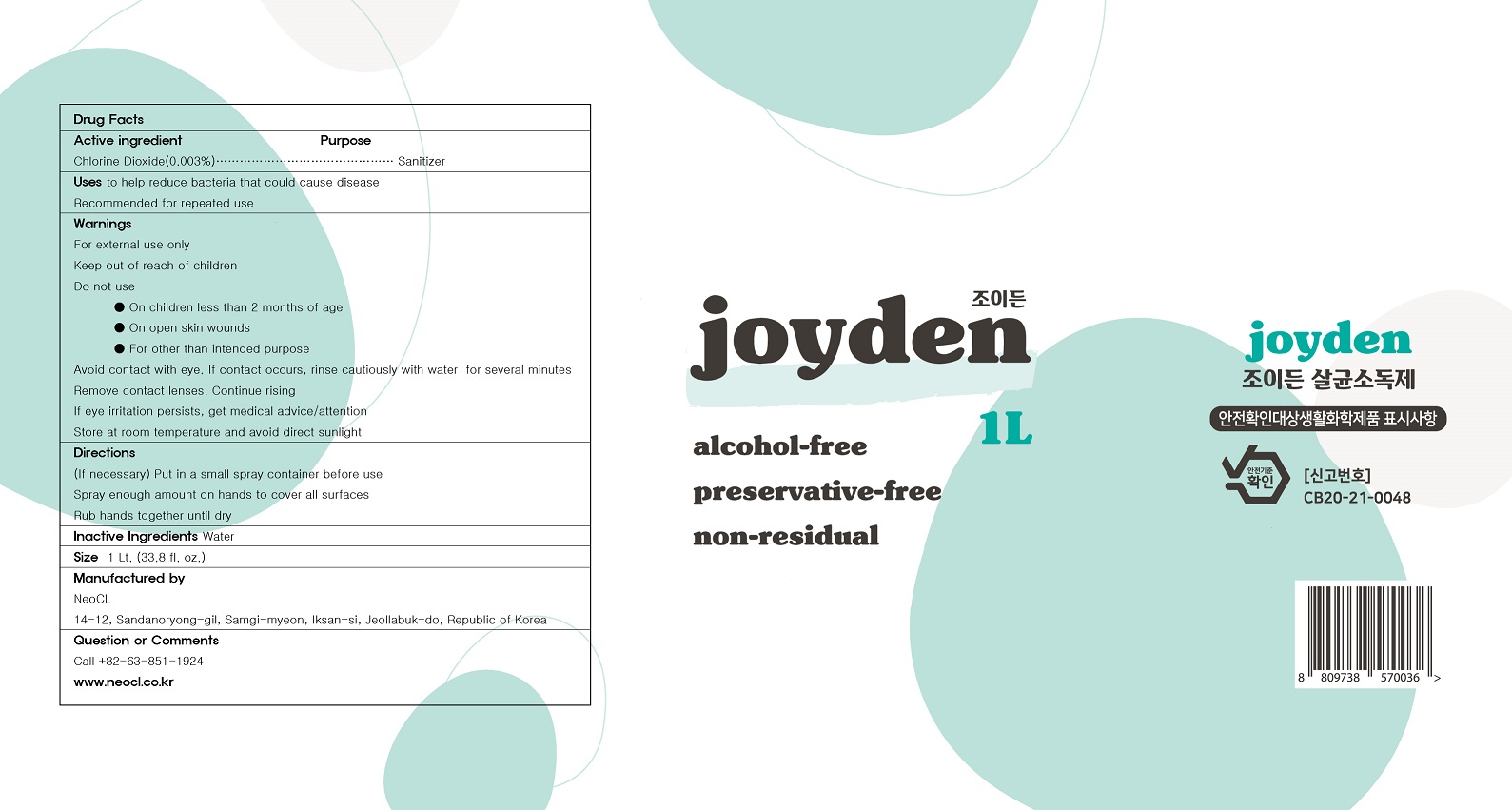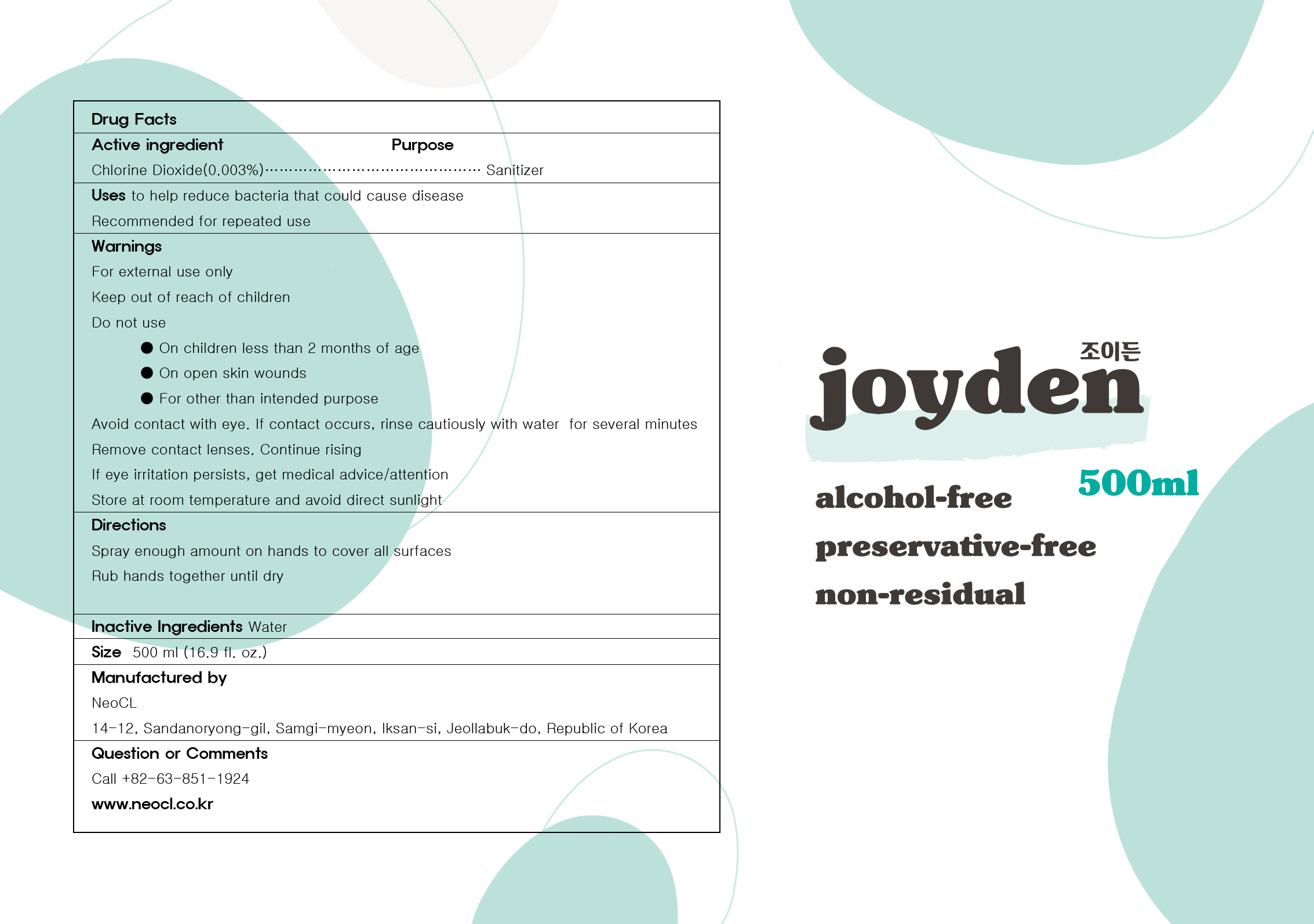 DRUG LABEL: Joyden
NDC: 76769-0003 | Form: LIQUID
Manufacturer: Private company NEOCL
Category: otc | Type: HUMAN OTC DRUG LABEL
Date: 20201027

ACTIVE INGREDIENTS: CHLORINE DIOXIDE 0.003 g/100 mL
INACTIVE INGREDIENTS: WATER

Drug Facts

ACTIVE INGREDIENT

Chlorine dioxide

INACTIVE INGREDIENT

Water

KEEP OUT OF REACH OF THE CHILDREN

PURPOSE

To help reduce bacteria that could cause disease

INDICATIONS AND USAGE

Place enough product on hands to cover all surfaces.Rub hands together until dry.
Supervise children under 6 years of age when using this product to avoid swallowing.

WARNINGS

For external use only

Keep out of reach of children

Do not use

In children less than 2 months of age

On open skin wounds

For other than intended purpose

Avoid contact with eye. If contact occurs, rinse cautiously with water for several minutes.

Remove contact lenses. Continue rising.

If eye irritation persists, get medical advice/attention.

Store at room temperature and avoid direct sunlight

DOSAGE AND ADMINISTRATION

for external use only